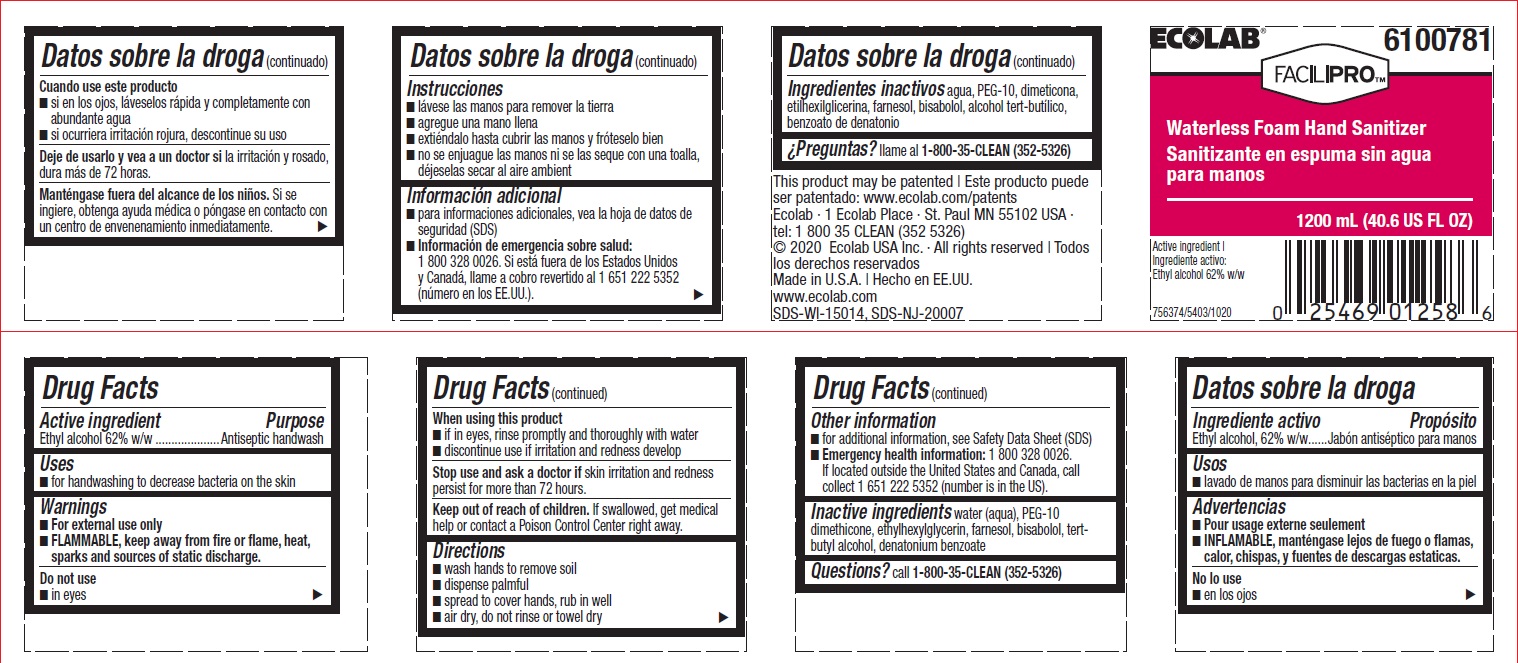 DRUG LABEL: Facilipro 
NDC: 47593-563 | Form: SOLUTION
Manufacturer: Ecolab Inc.
Category: otc | Type: HUMAN OTC DRUG LABEL
Date: 20240801

ACTIVE INGREDIENTS: Alcohol 620 mg/1 mL
INACTIVE INGREDIENTS: WATER; BIS-PEG-12 DIMETHICONE (500 MPA.S); ETHYLHEXYLGLYCERIN; FARNESOL; .ALPHA.-BISABOLOL, (+/-)-; TERT-BUTYL ALCOHOL; DENATONIUM BENZOATE

Drug Facts

Active ingredient

Ethyl alcohol, 62% w/w

Purpose

Antiseptic handwash

Uses

- For hand washing to decrease bacteria on the skin

Warnings

For external use only
Flammable, keep away from fire or flame, heat, sparks and sources of static discharge.

Do not use

- in eyes

When using this product

- if in eyes, rinse promptly and thoroughly with water
- discontinue use if irritation and redness develop

Stop use and ask a doctor if

- skin irritation and redness persist for more than 72 hours

Keep out of reach of children. If swallowed, get medical help or contact a Poison Control Center right away.

Directions

- wash hands to remove soil
- dispense palmful
- spread to cover hands, rub in well
- air dry, do not rinse or towel dry

Other information

- for additional information, see Material Safety Data Sheet (MSDS)
- Emergency health information: 1 800 328 0026. If located outside the United States and Canada, call collect 1 651 222 5352 (number is in the US).

INACTIVE INGREDIENT

Inactive ingredeints water (aqua), PEG-10 dimethicone, ethylhexylglycerin, farnesol, bisabolol, tert-butyl alcohol, dentonium benzoate

Questions? call 1-800-35-CLEAN (352-5326)

Principal Display Panel and Representative label

ECOLAB®

6100781

FACILIPRO™

Waterless Foam Hand Sanitizer

Sanitizante en espuma sin agua para manos

1200 mL (40.6 US FL OZ)

Active Ingredient:

Ethyl alcohol 62% w/w

Ecolab · 1 Ecolab Place · St. Paul MN 55102 USA · tel: 1 800 35 CLEAN (352 5326)

© 2020 Ecolab USA Inc. · All rights reserved | Todos los derechos reservados

Made in U.S.A. | Hecho en EE.UU.

www.ecolab.com

SDS-WI-15014, SDS-NJ-20007